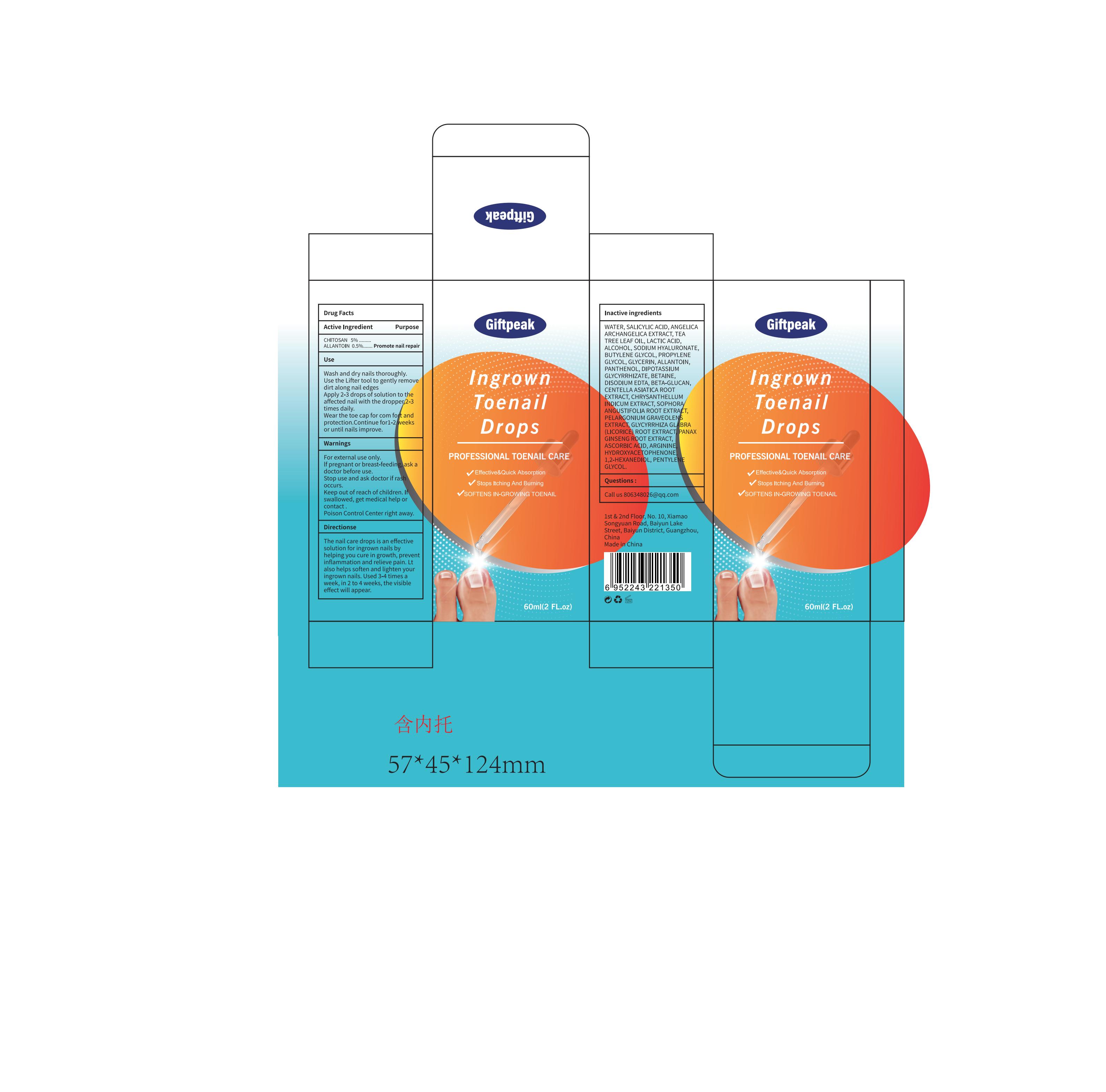 DRUG LABEL: Ingrown Toenail Drops
NDC: 60771-0007 | Form: OIL
Manufacturer: Guangzhou Haishi Biological Technology Co., Ltd.
Category: otc | Type: HUMAN OTC DRUG LABEL
Date: 20241207

ACTIVE INGREDIENTS: POLIGLUSAM 5 g/100 mL; ALLANTOIN 0.5 g/100 mL
INACTIVE INGREDIENTS: LACTIC ACID; SALICYLIC ACID; SODIUM HYALURONATE; ALCOHOL

Giftpeak Ingrown Toenail Drops

Active ingredients

CHITOSAN 5%

ALLANTOIN 0.5%

Purpose

The nail care drops is an effectivesolution for ingrown nails byhelping you cure in growth, preventinflammation and relieve pain. Ltalso helps soften and lighten youringrown nails. Used 3-4 times aweek, in 2 to 4 weeks, the visibleeffect will appear.

Uses

Wash and dry nails thoroughly.Use the Lifter tool to gently removedirt along nail edgesApply 2-3 drops of solution to theaffected nail with the droppeg2-3times daily.Wear the toe cap for com fort andprotection.Continue for1-2veeksor until nails improve.

Warnings

For external use only.

Stop use and ask a doctor if

rash occurs.

Do not use

If pregnant or breast-feeding,ask adoctor before use

When using this product

keep out of eyes. Rinse with water to remove.

Keep out of reach of children.

If swallowed, get medical help or contact a Poison Control Center right away.

Dosage

Apply 2-3 drops of solution to theaffected nail with the droppeg 2-3 times daily.

Inactive ingredients

WATER 53.15%
SALICYLIC ACID 2%
ANGELICA ARCHANGELICA EXTRACT 1%
TEA TREE LEAF OIL 1%
LACTIC ACID 2%
ALCOHOL 5%
SODIUM HYALURONATE 0.3%
BUTYLENE GLYCOL 3%
PROPYLENE GLYCOL 3%
GLYCERIN 3%
PANTHENOL 2%
DIPOTASSIUM GLYCYRRHIZATE 0.3%
BETAINE 1%
DISODIUM EDTA 0.05%
BETA-GLUCAN 2%
CENTELLA ASIATICA ROOT EXTRACT 2% CHRYSANTHELLUM INDICUM EXTRACT 2%
SOPHORA ANGUSTIFOLIA ROOT EXTRACT 2% PELARGONIUM GRAVEOLENS EXTRACT 2%
GLYCYRRHIZA GLABRA (LICORICE) ROOT EXTRACT 2%
PANAX GINSENG ROOT EXTRACT 2%
ASCORBIC ACID 2%
ARGININE 0.2%
HYDROXYACETOPHENONE 0.5%
1,2-HEXANEDIOL 0.5%
PENTYLENE GLYCOL 0.5%